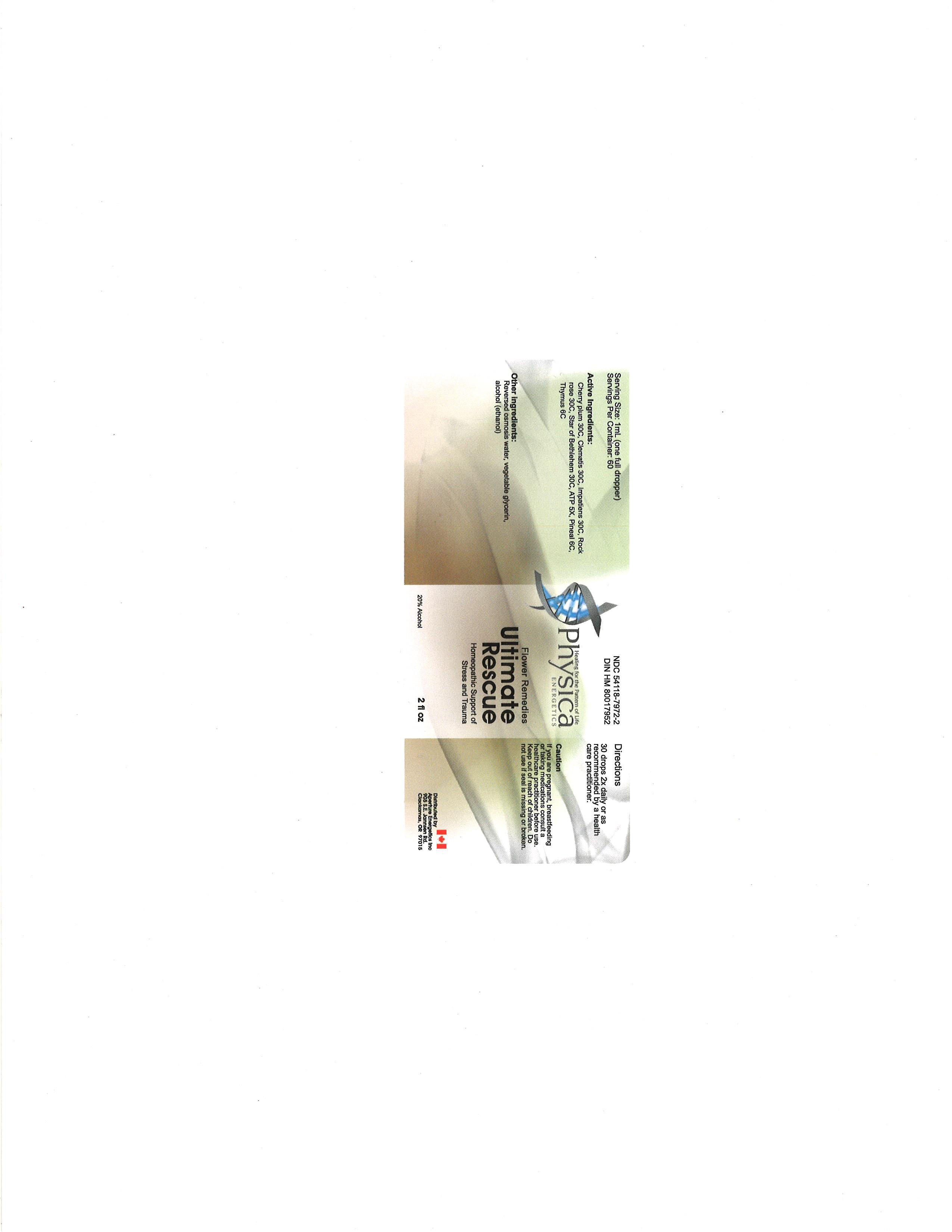 DRUG LABEL: Ultimate Rescue
NDC: 54118-7972 | Form: SOLUTION/ DROPS
Manufacturer: ABCO Laboratories, Inc.
Category: homeopathic | Type: HUMAN OTC DRUG LABEL
Date: 20121012

ACTIVE INGREDIENTS: CHERRY PLUM 30 [hp_C]/60 mL; CLEMATIS CHINENSIS ROOT 30 [hp_C]/60 mL; IMPATIENS BALSAMINA LEAF 30 [hp_C]/60 mL; CISTUS INCANUS WHOLE 30 [hp_C]/60 mL; ORNITHOGALUM UMBELLATUM 30 [hp_C]/60 mL; ADENOSINE TRIPHOSPHATE 5 [hp_X]/60 mL; BOS TAURUS PINEAL GLAND 6 [hp_C]/60 mL; BOS TAURUS THYMUS 6 [hp_C]/60 mL
INACTIVE INGREDIENTS: WATER; GLYCERIN; ALCOHOL

Ultimate Rescue Homeopathic

Active Ingredients:

Cherry plum 30C

Clematis 30C

Impatiens 30C

Rock rose 30C

Star of Bethlehem 30C

ATP 5X

Pineal 6C

Thymus 6C

PURPOSE

Support of Stress and Trauma

Keep out of reach of children

Directions:

30 drops 2X daily or as recommended by a health care practitioner

WARNINGS

If you are pregnant, breastfeeding or taking medications consult a healthcare practitioner before use.

Keep out of reach of children.

Do not use if seal is missing or broken.

INACTIVE INGREDIENT

Reversed osmosis water

vegetable glycerin

alcohol (ethanol)

bottle label.jpg

image of bottle label

DOSAGE AND ADMINISTRATION

30 drops 2X daily or as recommended by a health care practitioner